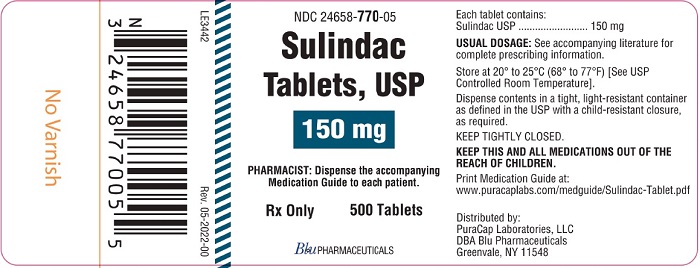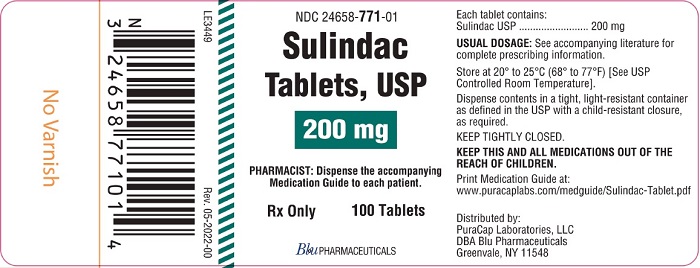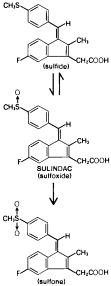 DRUG LABEL: SULINDAC
NDC: 24658-770 | Form: TABLET
Manufacturer: PuraCap Laboratories LLC dba Blu Pharmaceuticals
Category: prescription | Type: HUMAN PRESCRIPTION DRUG LABEL
Date: 20251211

ACTIVE INGREDIENTS: SULINDAC 150 mg/1 1
INACTIVE INGREDIENTS: SODIUM STARCH GLYCOLATE TYPE A POTATO; MAGNESIUM STEARATE; MICROCRYSTALLINE CELLULOSE; POVIDONE K30

Sulindac Tablets USP, 150 mg and 200 mg Rx only

BOXED WARNING

Cardiovascular Thrombotic Events

- Nonsteroidal anti-inflammatory drugs (NSAIDs) cause an increased risk of serious cardiovascular thrombotic events, including myocardial infarction and stroke, which can be fatal. This risk may occur early in treatment and may increase with duration of use (see WARNINGS and PRECAUTIONS).
- Sulindac tablets are contraindicated in the setting of coronary artery bypass graft (CABG) surgery (see CONTRAINDICATIONS and WARNINGS).

Gastrointestinal Risk

- NSAIDs cause an increased risk of serious gastrointestinal adverse events including bleeding, ulceration, and perforation of the stomach or intestines, which can be fatal. These events can occur at any time during use and without warning symptoms. Elderly patients are at greater risk for serious gastrointestinal events (See WARNINGS.)

DESCRIPTION

Sulindac is a non-steroidal, anti-inflammatory indene derivative designated chemically as (Z)-5-fluoro-2-methyl-1- [[p-(methylsulfinyl) phenyl]methylene] -1 H-indene-3-acetic acid. It is not a salicylate, pyrazolone or propionic acid derivative. Its empirical formula is C20H17FO3S, with a molecular weight of 356.42. Sulindac, a yellow crystalline compound, is a weak organic acid practically insoluble in water below pH 4.5, but very soluble as the sodium salt or in buffers of pH 6 or higher.

Sulindac is available in 150 and 200 mg tablets for oral administration. Each tablet contains the following inactive ingredients: magnesium stearate, microcrystalline cellulose, plasdone and sodium starch glycolate.

Following absorption, sulindac undergoes two major biotransformations - reversible reduction to the sulfide metabolite, and irreversible oxidation to the sulfone metabolite. Available evidence indicates that the biological activity resides with the sulfide metabolite.

The structural formulas of sulindac and its metabolites are:

CLINICAL PHARMACOLOGY

Pharmacodynamics

Sulindac is a non-steroidal anti-inflammatory drug (NSAID) that exhibits anti-inflammatory, analgesic and antipyretic activities in animal models. The mechanism of action, like that of other NSAIDs, is not completely understood but may be related to prostaglandin synthetase inhibition.

Pharmacokinetics

Absorption

The extent of sulindac absorption from Sulindac Tablets USP is similar as compared to sulindac solution.

There is no information regarding food effect on sulindac absorption. Antacids containing magnesium hydroxide 200 mg and aluminum hydroxide 225 mg per 5 mL have been shown not to significantly decrease the extent of sulindac absorption.

TABLE 1
PHARMACOKINETIC; PARAMETERS | NORMAL | ELDERLY
Tmax | Age 19-41 (n=24); (200 mg tablet); 3.38 ± 2.30 S; 4.88 ± 2.57 SP; 4.96 ± 2.36 SF; (150 mg tablet); 3.90 ± 2.30 S; 5.85 ± 4.49 SP; 6.15 ± 3.07 SF | Age 65-87 (n=12); (400 mg qd); 2.54 ± 1.52 S; 5.75 ± 2.81 SF; 6.83 ± 4.19 SP
Renal Clearance | (200 mg tablet); 68.12 ± 27.56 mL/min S; 36.58 ± 12.61 mL/min SP; (150 mg tablet); 74.39 ± 34.15 mL/min S; 41.75 ± 13.72 mL/min SP
Mean effective Half life (h) | 7.8 S; 16.4 SF
 | S = Sulindac; SF = Sulindac Sulfide; SP = Sulindac Sulfone

Distribution

Sulindac, and its sulfone and sulfide metabolites, are 93.1, 95.4, and 97.9% bound to plasma proteins, predominantly to albumin. Plasma protein binding measured over a concentration range (0.5-2.0 µg/mL) was constant. Following an oral, radiolabeled dose of sulindac in rats, concentrations of radiolabel in red blood cells were about 10% of those in plasma. Sulindac penetrates the blood-brain and placental barriers. Concentrations in brain did not exceed 4% of those in plasma. Plasma concentrations in the placenta and in the fetus were less than 25% and 5% respectively, of systemic plasma concentrations. Sulindac is excreted in rat milk; concentrations in milk were 10 to 20% of those levels in plasma. It is not known if sulindac is excreted in human milk.

Metabolism

Sulindac undergoes two major biotransformations of its sulfoxide moiety: oxidation to the inactive sulfone and reduction to the pharmacologically active sulfide. The latter is readily reversible in animals and in man. These metabolites are present as unchanged compounds in plasma and principally as glucuronide conjugates in human urine and bile. A dihydroxydihydro analog has also been identified as a minor metabolite in human urine.

With the twice-a-day dosage regimen, plasma concentrations of sulindac and its two metabolites accumulate: mean concentration over a dosage interval at steady state relative to the first dose averages 1.5 and 2.5 times higher, respectively, for sulindac and its active sulfide metabolite.

Sulindac and its sulfone metabolite undergo extensive enterohepatic circulation relative to the sulfide metabolite in animals. Studies in man have also demonstrated that recirculation of the parent drug sulindac and its sulfone metabolite is more extensive than that of the active sulfide metabolite. The active sulfide metabolite accounts for less than six percent of the total intestinal exposure to sulindac and its metabolites.

Biochemical as well as pharmacological evidence indicates that the activity of sulindac resides in its sulfide metabolite. An in-vitro assay for inhibition of cyclooxygenase activity exhibited an EC50 of 0.02µM for sulindac sulfide. In-vivo models of inflammation indicate that activity is more highly correlated with concentrations of the metabolite than with parent drug concentrations.

Elimination

Approximately 50% of the administered dose of sulindac is excreted in the urine with the conjugated sulfone metabolite accounting for the major portion. Less than 1% of the administered dose of sulindac appears in the urine as the sulfide metabolite. Approximately 25% is found in the feces, primarily as the sulfone and sulfide metabolites.

The mean effective half life (T1/2) is 7.8 and 16.4 hours, respectively, for sulindac and its active sulfide metabolite.

Because sulindac is excreted in the urine primarily as biologically inactive forms, it may possibly affect renal function to a lesser extent than other non-steroidal anti-inflammatory drugs; however, renal adverse experiences have been reported with sulindac (see ADVERSE REACTIONS).

In a study of patients with chronic glomerular disease treated with therapeutic doses of sulindac, no effect was demonstrated on renal blood flow, glomerular filtration rate, or urinary excretion of prostaglandin E2 and the primary metabolite of prostacyclin, 6-keto-PGF1α. However, in other studies in healthy volunteers and patients with liver disease, sulindac was found to blunt the renal responses to intravenous furosemide, i.e., the diuresis, natriuresis, increments in plasma renin activity and urinary excretion of prostaglandins. These observations may represent a differentiation of the effects of sulindac on renal functions based on differences in pathogenesis of the renal prostaglandin dependence associated with differing dose-response relationships of different NSAIDs to the various renal functions influenced by prostaglandins (see PRECAUTIONS).

In healthy men, the average fecal blood loss, measured over a two-week period during administration of 400 mg per day of sulindac, was similar to that for placebo, and was statistically significantly less than that resulting from 4800 mg per day of aspirin.]

Pediatric

The pharmacokinetics of sulindac have not been investigated in pediatric patients.

Race

Pharmacokinetic differences due to race have not been identified.

Hepatic Insufficiency

Patients with acute and chronic hepatic disease may require reduced doses of sulindac compared to patients with normal hepatic function since hepatic metabolism is an important elimination pathway.

Following a single dose, plasma concentrations of the active sulfide metabolite have been reported to be higher in patients with alcoholic liver disease compared to healthy normal subjects.

Renal Insufficiency

Sulindac pharmacokinetics have been investigated in patients with renal insufficiency. The disposition of sulindac was studied in end-stage renal disease patients requiring hemodialysis. Plasma concentrations of sulindac and its sulfone metabolite were comparable to those of normal healthy volunteers whereas concentrations of the active sulfide metabolite were significantly reduced. Plasma protein binding was reduced and the AUC of the unbound sulfide metabolite was about half that in healthy subjects.

Sulindac and its metabolites are not significantly removed from the blood in patients undergoing hemodialysis.

Since sulindac is eliminated primarily by the kidneys, patients with significantly impaired renal function should be closely monitored.

A lower daily dosage should be anticipated to avoid excessive drug accumulation.

In controlled clinical studies sulindac was evaluated in the following five conditions:

1. Osteoarthritis

In patients with osteoarthritis of the hip and knee, the anti-inflammatory and analgesic activity of sulindac was demonstrated by clinical measurements that included: assessments by both patient and investigator of overall response; decrease in disease activity as assessed by both patient and investigator; improvement in ARA Functional Class; relief of night pain; improvement in overall evaluation of pain, including pain on weight bearing and pain on active and passive motion; improvement in joint mobility, range of motion, and functional activities; decreased swelling and tenderness; and decreased duration of stiffness following prolonged inactivity.

In clinical studies in which dosages were adjusted according to patient needs, sulindac, 200 to 400 mg daily was shown to be comparable in effectiveness to aspirin 2400 to 4800 mg daily. Sulindac was generally well tolerated, and patients on it had a lower overall incidence of total adverse effects, of milder gastrointestinal reactions, and of tinnitus than did patients on aspirin. (See ADVERSE REACTIONS.)

2. Rheumatoid arthritis

In patients with rheumatoid arthritis, the anti-inflammatory and analgesic activity of sulindac was demonstrated by clinical measurements that included: assessments by both patient and investigator of overall response; decrease in disease activity as assessed by both patient and investigator; reduction in overall joint pain; reduction in duration and severity of morning stiffness; reduction in day and night pain; decrease in time required to walk 50 feet; decrease in general pain as measured on a visual analog scale; improvement in the Ritchie articular index; decrease in proximal interphalangeal joint size; improvement in ARA Functional Class; increase in grip strength; reduction in painful joint count and score; reduction in swollen joint count and score; and increased flexion and extension of the wrist.

In clinical studies in which dosages were adjusted according to patient needs, sulindac 300 to 400 mg daily was shown to be comparable in effectiveness to aspirin 3600 to 4800 mg daily. Sulindac was generally well tolerated, and patients on it had a lower overall incidence of total adverse effects, of milder gastrointestinal reactions, and of tinnitus than did patients on aspirin (See ADVERSE REACTIONS.)

In patients with rheumatoid arthritis, sulindac may be used in combination with gold salts at usual dosage levels. In clinical studies, sulindac added to the regimen of gold salts usually resulted in additional symptomatic relief but did not alter the course of the underlying disease.

3. Ankylosing spondylitis

In patients with ankylosing spondylitis, the anti-inflammatory and analgesic activity of sulindac was demonstrated by clinical measurements that included: assessments by both patient and investigator of overall response; decrease in disease activity as assessed by both patient and investigator; improvement in ARA Functional Class; improvement in patient and investigator evaluation of spinal pain, tenderness and/or spasm; reduction in the duration of morning stiffness; increase in the time to onset of fatigue; relief of night pain; increase in chest expansion; and increase in spinal mobility evaluated by fingers-to-floor distance, occiput to wall distance, the Schober Test, and the Wright Modification of the Schober Test. In a clinical study in which dosages were adjusted according to patient need, sulindac 200 to 400 mg daily was as effective as indomethacin 75 to 150 mg daily. In a second study, sulindac 300 to 400 mg daily was comparable in effectiveness to phenylbutazone 400 to 600 mg daily. Sulindac was better tolerated than phenylbutazone (See ADVERSE REACTIONS.)

4. Acute painful shoulder(Acute subacromial bursitis/supraspinatus tendinitis)

In patients with acute painful shoulder (acute subacromial bursitis/supraspinatus tendinitis), the anti-inflammatory and analgesic activity of sulindac was demonstrated by clinical measurements that included: assessments by both patient and investigator of overall response; relief of night pain, spontaneous pain, and pain on active motion; decrease in local tenderness; and improvement in range of motion measured by abduction, and internal and external rotation. In clinical studies in acute painful shoulder, sulindac 300 to 400 mg daily and oxyphenbutazone 400 to 600 mg daily were shown to be equally effective and well tolerated.

5. Acute gouty arthritis

In patients with acute gouty arthritis, the anti-inflammatory and analgesic activity of sulindac was demonstrated by clinical measurements that included: assessments by both the patient and investigator of overall response; relief of weight-bearing pain; relief of pain at rest and on active and passive motion; decrease in tenderness; reduction in warmth and swelling; increase in range of motion; and improvement in ability to function. In clinical studies, sulindac at 400 mg daily and phenylbutazone at 600 mg daily were shown to be equally effective. In these short-term studies in which reduction of dosage was permitted according to response, both drugs were equally well tolerated.

INDICATIONS AND USAGE

Carefully consider the potential benefits and risks of sulindac and other treatment options before deciding to use sulindac. Use the lowest effective dose for the shortest duration consistent with individual patient treatment goals (see WARNINGS).

Sulindac is indicated for acute or long-term use in the relief of signs and symptoms of the following:

1. Osteoarthritis

2. Rheumatoid arthritis**

3. Ankylosing spondylitis

4. Acute painful shoulder (Acute subacromial bursitis/supraspinatus tendinitis)

5. Acute gouty arthritis

**The safety and effectiveness of sulindac tablets USP have not been established in rheumatoid arthritis patients who are designated in the American Rheumatism Association classification as Functional Class IV (incapacitated, largely or wholly bedridden, or confined to wheelchair, little or no self-care).

CONTRAINDICATIONS

Sulindac is contraindicated in patients with known hypersensitivity to sulindac or the excipients (see DESCRIPTION).

Sulindac should not be given to patients who have experienced asthma, urticaria, or allergic-type reactions after taking aspirin or other NSAIDs. Severe, rarely fatal, anaphylactic/anaphylactoid reactions to NSAIDs have been reported in such patients (see WARNINGS – Anaphylactic/Anaphylactoid Reactions, and PRECAUTIONS – Preexisting Asthma).

Sulindac is contraindicated in the setting of coronary artery bypass graft (CABG) surgery (see WARNINGS).

WARNINGS

CARDIOVASCULAR EFFECTS

Cardiovascular Thrombotic Events

Clinical trials of several COX-2 selective and nonselective NSAIDs of up to three years duration have shown an increased risk of serious cardiovascular (CV) thrombotic events, including myocardial infarction (MI) and stroke, which can be fatal. Based on available data, it is unclear that the risk for CV thrombotic events is similar for all NSAIDs. The relative increase in serious CV thrombotic events over baseline conferred by NSAID use appears to be similar in those with and without known CV disease or risk factors for CV disease. However, patients with known CV disease or risk factors had a higher absolute incidence of excess serious CV thrombotic events, due to their increased baseline rate. Some observational studies found that this increased risk of serious CV thrombotic events began as early as the first weeks of treatment. The increase in CV thrombotic risk has been observed most consistently at higher doses.

To minimize the potential risk for an adverse CV event in NSAID-treated patients, use the lowest effective dose for the shortest duration possible. Physicians and patients should remain alert for the development of such events, throughout the entire treatment course, even in the absence of previous CV symptoms. Patients should be informed about the symptoms of serious CV events and the steps to take if they occur.

There is no consistent evidence that concurrent use of aspirin mitigates the increased risk of serious CV thrombotic events associated with NSAID use. The concurrent use of aspirin and an NSAID, such as sulindac, increases the risk of serious gastrointestinal (GI) events (see WARNINGS).

Status Post Coronary Artery Bypass Graft (CABG) Surgery

Two large, controlled clinical trials of a COX-2 selective NSAID for the treatment of pain in the first 10-14 days following CABG surgery found an increased incidence of myocardial infarction and stroke. NSAIDs are contraindicated in the setting of CABG (see CONTRAINDICATIONS).

Post-MI Patients

Observational studies conducted in the Danish National Registry have demonstrated that patients treated with NSAIDs in the post-MI period were at increased risk of reinfarction, CV-related death, and all-cause mortality beginning in the first week of treatment. In this same cohort, the incidence of death in the first year post MI was 20 per 100 person years in NSAID-treated patients compared to 12 per 100 person years in non-NSAID exposed patients. Although the absolute rate of death declined somewhat after the first year post-MI, the increased relative risk of death in NSAID users persisted over at least the next four years of follow-up.

Avoid the use of sulindac tablets, in patients with recent MI unless the benefits are expected to outweigh the risk of recurrent CV thrombotic events. If sulindac tablets are used in patients with a recent MI, monitor patients for signs of cardiac ischemia.

Hypertension

NSAIDs, including sulindac, can lead to onset of new hypertension or worsening of pre-existing hypertension, either of which may contribute to the increased incidence of CV events. Patients taking thiazides or loop diuretics may have impaired response to these therapies when taking NSAIDs. NSAIDs, including sulindac, should be used with caution in patients with hypertension. Blood pressure (BP) should be monitored closely during the initiation of NSAID treatment and throughout the course of therapy.

Heart Failure and Edema

The Coxib and traditional NSAID Trialists’ Collaboration meta-analysis of randomized controlled trials demonstrated an approximately two-fold increase in hospitalizations for heart failure in COX-2 selective-treated patients and nonselective NSAID-treated patients compared to placebo-treated patients. In a Danish National Registry study of patients with heart failure, NSAID use increased the risk of MI, hospitalization for heart failure, and death.

Additionally, fluid retention and edema have been observed in some patients treated with NSAIDs. Use of sulindac may blunt the CV effects of several therapeutic agents used to treat these medical conditions [e.g., diuretics, ACE inhibitors, or angiotensin receptor blockers (ARBs)] (see Drug Interactions).

Avoid the use of sulindac tablets in patients with severe heart failure unless the benefits are expected to outweigh the risk of worsening heart failure. If sulindac tablets are used in patients with severe heart failure, monitor patients for signs of worsening heart failure.

Gastrointestinal Effects – Risk of Ulceration, Bleeding, and Perforation

NSAIDs, including sulindac, can cause serious gastrointestinal (GI) adverse events including inflammation, bleeding, ulceration, and perforation of the stomach, small intestine, or large intestine, which can be fatal. These serious adverse events can occur at any time, with or without warning symptoms, in patients treated with NSAIDs. Only one in five patients, who develop a serious upper GI adverse event on NSAID therapy, is symptomatic.

Upper GI ulcers, gross bleeding, or perforation caused by NSAIDs occur in approximately 1% of patients treated for 3-6 months, and in about 2-4% of patients treated for one year. These trends continue with longer duration of use, increasing the likelihood of developing a serious GI event at some time during the course of therapy. However, even short-term therapy is not without risk.

NSAIDs should be prescribed with extreme caution in those with prior history of ulcer disease or gastrointestinal bleeding. Patients with a prior history of peptic ulcer disease and/or gastrointestinal bleeding who use NSAIDs have a greater than 10-fold increased risk for developing a GI bleed compared to patients with neither of these risk factors. Other factors that increase the risk for GI bleeding in patients treated with NSAIDs include concomitant use of oral corticosteroids or anticoagulants, longer duration of NSAID therapy, smoking, use of alcohol, older age, and poor general health status. Most spontaneous reports of fatal GI events are in elderly or debilitated patients and therefore, special care should be taken in treating this population.

To minimize the potential risk for an adverse GI event in patients treated with an NSAID, the lowest effective dose should be used for the shortest possible duration. Patients and physicians should remain alert for signs and symptoms of GI ulceration and bleeding during NSAID therapy and promptly initiate additional evaluation and treatment if a serious GI adverse event is suspected. This should include discontinuation of the NSAID until a serious GI adverse event is ruled out. For high risk patients, alternate therapies that do not involve NSAIDs should be considered.

Hepatic Effects

In addition to hypersensitivity reactions involving the liver, in some patients the findings are consistent with those of cholestatic hepatitis (see WARNINGS,Hypersensitivity). As with other non-steroidal anti-inflammatory drugs, borderline elevations of one or more liver tests without any other signs and symptoms may occur in up to 15% of patients taking NSAIDs including sulindac. These laboratory abnormalities may progress, may remain essentially unchanged, or may be transient with continued therapy. The SGPT (ALT) test is probably the most sensitive indicator of liver dysfunction. Meaningful (3 times the upper limit of normal) elevations of SGPT or SGOT (AST) occurred in controlled clinical trials in less than 1% of patients. Notable elevations of ALT or AST (approximately three or more times the upper limit of normal) have been reported in approximately 1% of patients in clinical trials with NSAIDs. In addition, rare cases of severe hepatic reactions, including jaundice and fatal fulminant hepatitis, liver necrosis and hepatic failure, some of them with fatal outcomes have been reported.

A patient with symptoms and/or signs suggesting liver dysfunction, or in whom an abnormal liver test has occurred, should be evaluated for evidence of the development of a more severe hepatic reaction while on therapy with sulindac. Although such reactions as described above are rare, if abnormal liver tests persist or worsen, if clinical signs and symptoms consistent with liver disease develop, or if systemic manifestations occur (e.g., eosinophilia, rash, etc.), sulindac should be discontinued.

In clinical trials with sulindac, the use of doses of 600 mg/day has been associated with an increased incidence of mild liver test abnormalities (see DOSAGE AND ADMINISTRATION for maximum dosage recommendation).

Renal Effects

Long-term administration of NSAIDs has resulted in renal papillary necrosis and other renal injury. Renal toxicity has also been seen in patients in whom renal prostaglandins have a compensatory role in the maintenance of renal perfusion.In these patients, administration of a non-steroidal anti-inflammatory drug may cause a dose-dependent reduction in prostaglandin formation and, secondarily, in renal blood flow, which may precipitate overt renal decompensation. Patients at greatest risk of this reaction are those with impaired renal function, heart failure, liver dysfunction, those taking diuretics and ACE inhibitors, patients who are volume-depleted, and the elderly. Discontinuation of NSAID therapy is usually followed by recovery to the pretreatment state.

Advanced Renal Disease

No information is available from controlled clinical studies regarding the use of sulindac in patients with advanced renal disease. Therefore, treatment with sulindac is not recommended in these patients with advanced renal disease. If sulindac therapy must be initiated, close monitoring of the patient’s renal function is advisable.

Anaphylactic/Anaphylactoid Reactions

As with other NSAIDs, anaphylactic/anaphylactoid reactions may occur in patients without known prior exposure to sulindac. Sulindac should not be given to patients with the aspirin triad. This symptom complex typically occurs in asthmatic patients who experience rhinitis with or without nasal polyps, or who exhibit severe, potentially fatal bronchospasm after taking aspirin or other NSAIDs (see CONTRAINDICATIONS and PRECAUTIONS – Preexisting Asthma). Emergency help should be sought in cases where an anaphylactic/anaphylactoid reaction occurs.

Serious Skin Reactions

NSAIDs, including sulindac, can cause serious adverse events such as exfoliative dermatitis, Stevens-Johnson Syndrome (SJS), and toxic epidermal necrolysis (TEN), which can be fatal. NSAIDs can also cause fixed drug eruption (FDE). FDE may present as a more severe variant known as generalized bullous fixed drug eruption (GBFDE), which can be life-threatening. These serious events may occur without warning. Inform patients about the signs and symptoms of serious skin reactions, and to discontinue the use of sulindac at the first appearance of skin rash or any other sign of hypersensitivity. Sulindac is contradicted in patients with previous serious skin reactions to NSAIDs (see CONTRAINDICATIONS).

Drug Reaction with Eosinophilia and Systemic Symptoms (DRESS) has been reported in patients taking NSAIDs such as sulindac. Some of these events have been fatal or life-threatening. DRESS typically, although not exclusively, presents with fever, rash, lymphadenopathy, and/or facial swelling. Other clinical manifestations may include hepatitis, nephritis, hematological abnormalities, myocarditis, or myositis. Sometimes symptoms of DRESS may resemble an acute viral infection. Eosinophilia is often present. Because this disorder is variable in its presentation, other organ systems not noted here may be involved. It is important to note that early manifestations of hypersensitivity, such as fever or lymphadenopathy, may be present even though rash is not evident. If such signs or symptoms are present, discontinue sulindac and evaluate the patient immediately.

Hypersensitivity

Rarely, fever and other evidence of hypersensitivity (see ADVERSE REACTIONS) including abnormalities in one or more liver function tests and severe skin reactions have occurred during therapy with sulindac. Fatalities have occurred in these patients. Hepatitis, jaundice, or both, with or without fever, may occur usually within the first one to three months of therapy. Determinations of liver function should be considered whenever a patient on therapy with sulindac develops unexplained fever, rash or other dermatologic reactions or constitutional symptoms. If unexplained fever or other evidence of hypersensitivity occurs, therapy with sulindac should be discontinued. The elevated temperature and abnormalities in liver function caused by sulindac characteristically have reverted to normal after discontinuation of therapy. Administration of sulindac should not be reinstituted in such patients.

Fetal Toxicity

Premature Closure of Fetal Ductus Arteriosus:

Avoid use of NSAIDs, including sulindac, in pregnant women at about 30 weeks gestation and later. NSAIDs including sulindac, increase the risk of premature closure of the fetal ductus arteriosus at approximately this gestational age.

Oligohydramnios/Neonatal Renal Impairment:

Use of NSAIDs, including sulindac, at about 20 weeks gestation or later in pregnancy may cause fetal renal dysfunction leading to oligohydramnios and, in some cases, neonatal renal impairment. These adverse outcomes are seen, on average, after days to weeks of treatment, although oligohydramnios has been infrequently reported as soon as 48 hours after NSAID initiation. Oligohydramnios is often, but not always, reversible with treatment discontinuation. Complications of prolonged oligohydramnios may, for example, include limb contractures and delayed lung maturation. In some postmarketing cases of impaired neonatal renal function, invasive procedures such as exchange transfusion or dialysis were required.

If NSAID treatment is necessary between about 20 weeks and 30 weeks gestation, limit sulindac use to the lowest effective dose and shortest duration possible. Consider ultrasound monitoring of amniotic fluid if sulindac treatment extends beyond 48 hours. Discontinue sulindac if oligohydramnios occurs and follow up according to clinical practice (see PRECAUTIONS; Pregnancy).

PRECAUTIONS

General

Sulindac cannot be expected to substitute for corticosteroids or to treat corticosteroid insufficiency. Abrupt discontinuation of corticosteroids may lead to disease exacerbation. Patients on prolonged corticosteroid therapy should have their therapy tapered slowly if a decision is made to discontinue corticosteroids.

The pharmacological activity of sulindac in reducing fever and inflammation may diminish the utility of these diagnostic signs in detecting complications of presumed noninfectious, painful conditions.

Hematological Effects

Anemia is sometimes seen in patients receiving NSAIDs, including sulindac. This may be due to fluid retention, occult or gross GI blood loss, or an incompletely described effect upon erythropoiesis. Patients on long-term treatment with NSAIDs, including sulindac, should have their hemoglobin or hematocrit checked if they exhibit any signs or symptoms of anemia.

NSAIDs inhibit platelet aggregation and have been shown to prolong bleeding time in some patients. Unlike aspirin, their effect on platelet function is quantitatively less, of shorter duration, and reversible. Patients receiving sulindac who may be adversely affected by alterations in platelet function, such as those with coagulation disorders or patients receiving anticoagulants, should be carefully monitored.

Preexisting Asthma

Patients with asthma may have aspirin-sensitive asthma. The use of aspirin in patients with aspirin-sensitive asthma has been associated with severe bronchospasm which can be fatal. Since cross reactivity, including bronchospasm, between aspirin and other non-steroidal anti-inflammatory drugs has been reported in such aspirin-sensitive patients, sulindac should not be administered to patients with this form of aspirin sensitivity and should be used with caution in patients with preexisting asthma.

Renal Calculi

Sulindac metabolites have been reported rarely as the major or a minor component in renal stones in association with other calculus components. Sulindac should be used with caution in patients with a history of renal lithiasis, and they should be kept well hydrated while receiving sulindac.

Pancreatitis

Pancreatitis has been reported in patients receiving sulindac (see ADVERSE REACTIONS). Should pancreatitis be suspected, the drug should be discontinued and not restarted, supportive medical therapy instituted, and the patient monitored closely with appropriate laboratory studies (e.g., serum and urine amylase, amylase/creatinine clearance ratio, electrolytes, serum calcium, glucose, lipase, etc.). A search for other causes of pancreatitis as well as those conditions which mimic pancreatitis should be conducted.

Ocular Effects

Because of reports of adverse eye findings with non-steroidal anti-inflammatory agents, it is recommended that patients who develop eye complaints during treatment with sulindac have ophthalmologic studies.

Hepatic Insufficiency

In patients with poor liver function, delayed, elevated and prolonged circulating levels of the sulfide and sulfone metabolites may occur. Such patients should be monitored closely; a reduction of daily dosage may be required.

SLE and Mixed Connective Tissue Disease

In patients with systemic lupus erythematosus (SLE) and mixed connective tissue disease, there may be an increased risk of aseptic meningitis (see ADVERSE REACTIONS).

Information for Patients

Patients should be informed of the following information before initiating therapy with an NSAID and periodically during the course of ongoing therapy. Patients should also be encouraged to read the NSAID Medication Guide that accompanies each prescription dispensed.

1. Cardiovascular Thrombotic Events
  Advise patients to be alert for the symptoms of cardiovascular thrombotic events, including chest pain, shortness of breath, weakness, or slurring of speech, and to report any of these symptoms to their healthcare provider immediately (see WARNINGS).
2. Sulindac, like other NSAIDs, can cause GI discomfort and, rarely, serious GI side effects, such as ulcers and bleeding, which may result in hospitalization and even death. Although serious GI tract ulcerations and bleeding can occur without warning symptoms, patients should be alert for the signs and symptoms of ulcerations and bleeding, and should ask for medical advice when observing any indicative sign or symptoms including epigastric pain, dyspepsia, melena, and hematemesis. Patients should be apprised of the importance of this follow-up (see WARNINGS, Gastrointestinal Effects – Risk of Ulceration, Bleeding, and Perforation).
3. Serious Skin Reactions, including DRESS
  Advise patients to stop taking sulindac immediately if they develop any type of rash or fever and to contact their healthcare provider as soon as possible (see WARNINGS).
4. Heart Failure and Edema:Advise patients to be alert for the symptoms of congestive heart failure including shortness of breath, unexplained weight gain, or edema and to contact their healthcare provider if such symptoms occur (see WARNINGS).
5. Patients should be informed of the warning signs and symptoms of hepatotoxicity (e.g., nausea, fatigue, lethargy, pruritus, jaundice, right upper quadrant tenderness, and “flu-like” symptoms). If these occur, patients should be instructed to stop therapy and seek immediate medical therapy.
6. Patients should be informed of the signs of an anaphylactic/anaphylactoid reaction (e.g., difficulty breathing, swelling of the face or throat). If these occur, patients should be instructed to seek immediate emergency help (see WARNINGS).
7. Fetal Toxicity
  Inform pregnant women to avoid use of sulindac and other NSAIDs starting at 30 weeks gestation because of the risk of the premature closing of the fetal ductus arteriosus. If treatment with sulindac is needed for a pregnant woman between about 20 to 30 weeks gestation, advise her that she may need to be monitored for oligohydramnios, if treatment continues for longer than 48 hours (see WARNINGS;
  Fetal Toxicity, PRECAUTIONS; Pregnancy).

Laboratory Tests

Because serious GI tract ulcerations and bleeding can occur without warning symptoms, physicians should monitor for signs or symptoms of GI bleeding. Patients on long-term treatment with NSAIDs should have their CBC and a chemistry profile checked periodically. If clinical signs and symptoms consistent with liver or renal disease develop, systemic manifestations occur (e.g., eosinophilia, rash, etc.) or if abnormal liver tests persist or worsen, sulindac should be discontinued.

Drug Interactions

ACE-Inhibitors and Angiotensin II Antagonists

Reports suggest that NSAIDs may diminish the antihypertensive effect of ACE-inhibitors and angiotensin II antagonists. These interactions should be given consideration in patients taking NSAIDs concomitantly with ACE-inhibitors or angiotensin II antagonists. In some patients with compromised renal function (e.g., elderly patients or patients who are volume-depleted, including those on diuretic therapy) who are being treated with non-steroidal anti-inflammatory drugs, the co-administration of an NSAID and an ACE-inhibitor or an angiotensin II antagonist may result in further deterioration of renal function, including possible acute renal failure, which is usually reversible. Therefore, monitor renal function periodically in patients receiving ACEIs or AIIAs and NSAIDs in combination therapy.

Acetaminophen

Acetaminophen had no effect on the plasma levels of sulindac or its sulfide metabolite.

Aspirin

The concomitant administration of aspirin with sulindac significantly depressed the plasma levels of the active sulfide metabolite. A double-blind study compared the safety and efficacy of sulindac 300 or 400 mg daily given alone or with aspirin 2.4 g/day for the treatment of osteoarthritis. The addition of aspirin did not alter the types of clinical or laboratory adverse experiences for sulindac; however, the combination showed an increase in the incidence of gastrointestinal adverse experiences. Since the addition of aspirin did not have a favorable effect on the therapeutic response to sulindac, the combination is not recommended.

Cyclosporine

Administration of non-steroidal anti-inflammatory drugs concomitantly with cyclosporine has been associated with an increase in cyclosporine-induced toxicity, possibly due to decreased synthesis of renal prostacyclin. NSAIDs should be used with caution in patients taking cyclosporine, and renal function should be carefully monitored.

Diflunisal

The concomitant administration of sulindac and diflunisal in normal volunteers resulted in lowering of the plasma levels of the active sulindac sulfide metabolite by approximately one-third.

Diuretics

Clinical studies, as well as post marketing observations, have shown that sulindac can reduce the natriuretic effect of furosemide and thiazides in some patients. This response has been attributed to inhibition of renal prostaglandin synthesis. During concomitant therapy with NSAIDs, the patient should be observed closely for signs of renal failure (see WARNINGS,Renal Effects), as well as to assure diuretic efficacy.

DMSO

DMSO should not be used with sulindac. Concomitant administration has been reported to reduce the plasma levels of the active sulfide metabolite and potentially reduce efficacy. In addition, this combination has been reported to cause peripheral neuropathy.

Lithium

NSAIDs have produced an elevation of plasma lithium levels and a reduction in renal lithium clearance. The mean minimum lithium concentration increased 15% and the renal clearance was decreased by approximately 20%. These effects have been attributed to inhibition of renal prostaglandin synthesis by the NSAID. Thus, when NSAIDs and lithium are administered concurrently, subjects should be observed carefully for signs of lithium toxicity.

Methotrexate

NSAIDs have been reported to competitively inhibit methotrexate accumulation in rabbit kidney slices. This may indicate that they could enhance the toxicity of methotrexate. Caution should be used when NSAIDs are administered concomitantly with methotrexate.

NSAIDs

The concomitant use of sulindac with other NSAIDs is not recommended due to the increased possibility of gastrointestinal toxicity, with little or no increase in efficacy.

Oral anticoagulants

Although sulindac and its sulfide metabolite are highly bound to protein, studies in which sulindac was given at a dose of 400 mg daily have shown no clinically significant interaction with oral anticoagulants. However, patients should be monitored carefully until it is certain that no change in their anticoagulant dosage is required. Special attention should be paid to patients taking higher doses than those recommended and to patients with renal impairment or other metabolic defects that might increase sulindac blood levels. The effects of warfarin and NSAIDs on GI bleeding are synergistic, such that users of both drugs together have a risk of serious GI bleeding higher than users of either drug alone.

Oral hypoglycemic agents

Although sulindac and its sulfide metabolite are highly bound to protein, studies in which sulindac was given at a dose of 400 mg daily, have shown no clinically significant interaction with oral hypoglycemic agents. However, patients should be monitored carefully until it is certain that no change in their hypoglycemic dosage is required. Special attention should be paid to patients taking higher doses than those recommended and to patients with renal impairment or other metabolic defects that might increase sulindac blood levels.

Probenecid

Probenecid given concomitantly with sulindac had only a slight effect on plasma sulfide levels, while plasma levels of sulindac and sulfone were increased. Sulindac was shown to produce a modest reduction in the uricosuric action of probenecid, which probably is not significant under most circumstances.

Propoxyphene hydrochloride

Propoxyphene hydrochloride had no effect on the plasma levels of sulindac or its sulfide metabolite.

Pregnancy

Risk Summary

Use of NSAIDs, including sulindac, can cause premature closure of the fetal ductus arteriosus and fetal renal dysfunction leading to oligohydramnios and, in some cases, neonatal renal impairment. Because of these risks, limit dose and duration of sulindac use between about 20 and 30 weeks of gestation, and avoid sulindac use at about 30 weeks of gestation and later in pregnancy (see WARNINGS; Fetal Toxicity).

Premature Closure of Fetal Ductus Arteriosus

Use of NSAIDs, including sulindac, at about 30 weeks gestation or later in pregnancy increases the risk of premature closure of the fetal ductus arteriosus.

Oligohydramnios/Neonatal Renal Impairment

Use of NSAIDs at about 20 weeks gestation or later in pregnancy has been associated with cases of fetal renal dysfunction leading to oligohydramnios, and in some cases, neonatal renal impairment.

Data from observational studies regarding other potential embryofetal risks of NSAID use in women in the first or second trimesters of pregnancy are inconclusive. In animal reproduction studies rats and rabbits have not demonstrated evidence of developmental abnormalities. However, animal reproduction studies are not always predictive of human response. There are no adequate and well-controlled studies in pregnant women. Sulindac should be used in pregnancy only if the potential benefit justifies the potential risk to the fetus. Based on animal data, prostaglandins have been shown to have an important role in endometrial vascular permeability, blastocyst implantation, and decidualization. In animal studies, administration of prostaglandin synthesis inhibitors such as sulindac, resulted in increased pre- and post-implantation loss. Prostaglandins also have been shown to have an important role in fetal kidney development. In published animal studies, prostaglandin synthesis inhibitors have
been reported to impair kidney development when administered at clinically relevant doses.

The estimated background risk of major birth defects and miscarriage for the indicated population(s) is unknown. All pregnancies have a background risk of birth defect, loss, or other adverse outcomes. In the U.S. general population, the estimated background risk of major birth defects and miscarriage in clinically recognized pregnancies is 2-4% and 15-20%, respectively.

Clinical Considerations

Fetal/Neonatal Adverse Reactions

Premature Closure of Fetal Ductus Arteriosus:

Avoid use of NSAIDs in women at about 30 weeks gestation and later in pregnancy, because NSAIDs, including sulindac, can cause premature closure of the fetal ductus arteriosus (see WARNINGS; Fetal Toxicity).

Oligohydramnios/Neonatal Renal Impairment

If an NSAID is necessary at about 20 weeks gestation or later in pregnancy, limit the use to the lowest effective dose and shortest duration possible. If sulindac treatment extends beyond 48 hours, consider monitoring with ultrasound for oligohydramnios. If oligohydramnios occurs, discontinue sulindac and follow up according to clinical practice (see WARNINGS; Fetal Toxicity).

Data

Human Data

There are no adequate, well-controlled studies in pregnant women. Sulindac tablets should be used in pregnancy only if the potential benefit justifies the potential risk to the fetus.

The known effect of drugs of this class on the human fetus during the third trimester of pregnancy include: constriction of the ductus arteriosus prenatally, tricuspid incompetence, and pulmonary hypertension; nonclosure of the ductus arteriosus postnatally which may be resistant to medical management; myocardial degenerative changes, platelet dysfunction with resultant bleeding, intracranial bleeding, renal dysfunction or failure, renal injury/dysgenesis which may result in prolonged or permanent renal failure, oligohydramnios, gastrointestinal bleeding or perforation, and increased risk of necrotizing enterocolitis.

Premature Closure of Fetal Ductus Arteriosus:

Published literature reports that the use of NSAIDs at about 30 weeks of gestation and later in pregnancy may cause premature closure of the fetal ductus arteriosus.

Oligohydramnios/Neonatal Renal Impairment:

Published studies and postmarketing reports describe maternal NSAID use at about 20 weeks gestation or later in pregnancy associated with fetal renal dysfunction leading to oligohydramnios, and in some cases, neonatal renal impairment. These adverse outcomes are seen, on average, after days to weeks of treatment, although oligohydramnios has been infrequently reported as soon as 48 hours after NSAID initiation. In many cases, but not all, the decrease in amniotic fluid was transient and reversible with cessation of the drug. There have been a limited number of case reports of maternal NSAID use and neonatal renal dysfunction without oligohydramnios, some of which were irreversible. Some cases of neonatal renal dysfunction required treatment with invasive procedures, such as exchange transfusion or dialysis.

Methodological limitations of these postmarketing studies and reports include lack of a control group; limited information regarding dose, duration, and timing of drug exposure; and concomitant use of other medications. These limitations preclude establishing a reliable estimate of the risk of adverse fetal and neonatal outcomes with maternal NSAID use. Because the published safety data on neonatal outcomes involved mostly preterm infants, the generalizability of certain reported risks to the full-term infant exposed to NSAIDs through maternal use is uncertain.

Labor and Delivery

In rat studies with NSAIDs, as with other drugs known to inhibit prostaglandin synthesis, an increased incidence of dystocia, delayed parturition, and decreased pup survival occurred. The effects of sulindac on labor and delivery in pregnant women are unknown.

Nursing Mothers

It is not known whether this drug is excreted in human milk; however, it is secreted in the milk of lactating rats. Because many drugs are excreted in human milk and because of the potential for serious adverse reactions in nursing infants from sulindac, a decision should be made whether to discontinue nursing or to discontinue the drug, taking into account the importance of the drug to the mother.

Pediatric Use

Safety and effectiveness in pediatric patients have not been established.

Geriatric Use

As with any NSAID, caution should be exercised in treating the elderly (65 years and older) since advancing age appears to increase the possibility of adverse reactions. Elderly patients seem to tolerate ulceration or bleeding less well than other individuals and many spontaneous reports of fatal GI events are in this population (see WARNINGS,Gastrointestinal Effects – Risk of Ulceration, Bleeding, and Perforation).

Sulindac is known to be substantially excreted by the kidney and the risk of toxic reactions to this drug may be greater in patients with impaired renal function. Because elderly patients are more likely to have decreased renal function, care should be taken in dose selection and it may be useful to monitor renal function (See WARNINGS, Renal Effects).

ADVERSE REACTIONS

The following adverse reactions were reported in clinical trials or have been reported since the drug was marketed. The probability exists of a causal relationship between sulindac and these adverse reactions. The adverse reactions which have been observed in clinical trials encompass observations in 1,865 patients, including 232 observed for at least 48 weeks.

Incidence Greater Than 1%

Gastrointestinal

The most frequent types of adverse reactions occurring with sulindac are gastrointestinal; these include gastrointestinal pain (10%), dyspepsia***, nausea*** with or without vomiting, diarrhea***, constipation***, flatulence, anorexia and gastrointestinal cramps.

Dermatologic

Rash***, pruritus

Central Nervous System

Dizziness***, headache***, nervousness.

Special Senses

Tinnitus.

Miscellaneous

Edema (see WARNINGS).

Incidence Less Than 1 in 100

Gastrointestinal

Gastritis, gastroenteritis or colitis. Peptic ulcer and gastrointestinal bleeding have been reported. GI perforation and intestinal strictures (diaphragms) have been reported rarely.
Liver function abnormalities; jaundice, sometimes with fever; cholestasis; hepatitis; hepatic failure.
There have been rare reports of sulindac metabolites in common bile duct “sludge” and in biliary calculi in patients with symptoms of cholecystitis who underwent a cholecystectomy.
Pancreatitis (see PRECAUTIONS).
Ageusia; glossitis.

Dermatologic

Stomatitis, sore or dry mucous membranes, alopecia, photosensitivity.
Erythema multiforme, toxic epidermal necrolysis, Stevens-Johnson syndrome, fixed drug eruption (FDE), and exfoliative dermatitis have been reported.

Cardiovascular

Congestive heart failure, especially in patients with marginal cardiac function; palpitation; hypertension.

Hematologic

Thrombocytopenia; ecchymosis, purpura, leukopenia, agranulocytosis, neutropenia, bone marrow depression, including aplastic anemia; hemolytic anemia, increased prothrombin time in patients on oral anticoagulants (see PRECAUTIONS).

Genitourinary

Urine discoloration; dysuria; vaginal bleeding, hematuria; proteinuria; crystalluria; renal impairment, including renal failure; interstitial nephritis; nephrotic syndrome.
Renal calculi containing sulindac metabolites have been observed rarely.

Metabolic

Hyperkalemia.

Musculoskeletal

Muscle weakness.

Psychiatric

Depression; psychic disturbances including acute psychosis.

Nervous System

Vertigo; insomnia; somnolence; paresthesia; convulsions; syncope; aseptic meningitis (especially in patients with systemic lupus erythematosus (SLE) and mixed connective tissue disease, see PRECAUTIONS).

Special Senses

Blurred vision; visual disturbances; decreased hearing; metallic or bitter taste.

Respiratory

Epistaxis.

Hypersensitivity Reactions

Anaphylaxis; angioneurotic edema; urticaria, bronchial spasm; dyspnea.
Hypersensitivity vasculitis.

A potentially fatal apparent hypersensitivity syndrome has been reported. This syndrome may include constitutional symptoms (fever, chills, diaphoresis, flushing), cutaneous findings (rash or other dermatologic reactions – see above), conjunctivitis, involvement of major organs (changes in liver function including hepatic failure, jaundice, pancreatitis, pneumonitis with or without pleural effusion, leukopenia, leukocytosis, eosinophilia, disseminated intravascular coagulation, anemia, renal impairment, including renal failure), and other less specific findings (adenitis, arthralgia, arthritis, myalgia, fatigue, malaise, hypotension, chest pain, tachycardia).

Causal Relationship Unknown

A rare occurrence of fulminant necrotizing fasciitis, particularly in association with Group A β-hemolytic streptococcus, has been described in persons treated with non-steroidal anti-inflammatory agents, sometimes with fatal outcome (see also PRECAUTIONS, General).

Other reactions have been reported in clinical trials or since the drug was marketed, but occurred under circumstances where a causal relationship could not be established. However, in these rarely reported events, that possibility cannot be excluded. Therefore, these observations are listed to serve as alerting information to physicians.

Cardiovascular

Arrhythmia.

Metabolic

Hyperglycemia.

Nervous System

Neuritis.

Special Senses

Disturbances of the retina and its vasculature.

Miscellaneous

Gynecomastia.

***Incidence between 3% and 9%. Those reactions occurring in 1% to 3% of patients are not marked with an asterisk.

MANAGEMENT OF OVERDOSAGE

Cases of overdosage have been reported and rarely, deaths have occurred. The following signs and symptoms may be observed following overdosage; stupor, coma, diminished urine output and hypotension.

In the event of overdosage, the stomach should be emptied by inducing vomiting or by gastric lavage, and the patient carefully observed and given symptomatic and supportive treatment.

Animal studies show that absorption is decreased by the prompt administration of activated charcoal and excretion is enhanced by alkalinization of the urine.

DOSAGE AND ADMINISTRATION

Carefully consider the potential benefits and risks of sulindac and other treatment options before deciding to use sulindac. Use the lowest effective dose for the shortest duration consistent with individual patient treatment goals (see WARNINGS).

After observing the response to initial therapy with Sulindac Tablets USP, the dose and frequency should be adjusted to suit an individual patient’s needs.

Sulindac Tablets should be administered orally twice a day with food. The maximum dosage is 400 mg per day. Dosages above 400 mg per day are not recommended.

In osteoarthritis, rheumatoid arthritis, and ankylosing spondylitis, the recommended starting dosage is 150 mg twice a day. The dosage may be lowered or raised depending on the response.

A prompt response (within one week) can be expected in about one-half of patients with osteoarthritis, ankylosing spondylitis, and rheumatoid arthritis. Others may require longer to respond. In acute painful shoulder (acute subacromial bursitis/supraspinatus tendinitis) and acute gouty arthritis, the recommended dosage is 200 mg twice a day. After a satisfactory response has been achieved, the dosage may be reduced according to the response. In acute painful shoulder, therapy for 7-14 days is usually adequate. In acute gouty arthritis, therapy for 7 days is usually adequate.

HOW SUPPLIED

Sulindac Tablets USP, 150 mg are yellow, round tablets, bisected and debossed with “Є” to the left of bisect and “10” to the right of bisect on one side, and plain on the other side. They are supplied as follows:

NDC 24658-770-01 Bottles of 100 Tablets

NDC 24658-770-05 Bottles of 500 Tablets

Sulindac Tablets USP, 200 mg are yellow, oval-shaped tablets, bisected and debossed with “Є” to the left of bisect and “11” to the right of bisect on one side, and plain on the other side. They are supplied as follows:

NDC 24658-771-01 Bottles of 100 Tablets

NDC 24658-771-05 Bottles of 500 Tablets

Storage

Store in a well-closed container at 20° to 25° C (68 to 77° F) [See USP Controlled Room Temperature].

Dispense with Medication Guide available at: www.puracaplabs.com/medguide/Sulindac-Tablet.pdf

Distributed by:

PuraCap Laboratories, LLC

DBA Blu Pharmaceuticals

Greenvale, NY 11548

Rev. 04-2025-00

MFBLU018REV04/25

OE2617

MEDICATION GUIDE

Dispense with Medication Guide available at: www.puracaplabs.com/medguide/Sulindac-Tablet.pdf

Medication Guide for Nonsteroidal Anti-Inflammatory Drugs (NSAIDs)

What is the most important information I should know about medicines called Nonsteroidal Anti-Inflammatory Drugs (NSAIDs)?

NSAIDs can cause serious side effects, including:

- Increased risk of a heart attack or stroke that can lead to death. This risk may happen early in treatment and may increase:
  - with increasing doses of NSAIDs
  - with longer use of NSAIDs

Do not take NSAIDs right before or after a heart surgery called a “coronary artery bypass graft (CABG).” Avoid taking NSAIDs after a recent heart attack, unless your healthcare provider tells you to. You may have an increased risk of another heart attack if you take NSAIDs after a recent heart attack.

- Increased risk of bleeding, ulcers, and tears (perforation) of the esophagus (tube leading from the mouth to the stomach), stomach and intestines:
-
  - anytime during use
  - without warning symptoms
  - that may cause death

The risk of getting an ulcer or bleeding increases with:

NSAIDs should only be used:

What are NSAIDs?

NSAIDs are used to treat pain and redness, swelling, and heat (inflammation) from medical conditions such as different types of arthritis, menstrual cramps, and other types of short-term pain.

Who should not take NSAIDs?

Do not take NSAIDs:

- if you have had an asthma attack, hives, or other allergic reaction with aspirin or any other NSAIDs.
- right before or after heart bypass surgery.

Before taking NSAIDs, tell your healthcare provider about all of your medical conditions, including if you:

- have liver or kidney problems
- have high blood pressure
- have asthma
- are pregnant or plan to become pregnant. Taking NSAIDs at about 20 weeks of pregnancy or later may harm your unborn baby. If you need to take NSAIDs for more than 2 days when you are between 20 and 30 weeks of pregnancy, your healthcare provider may need to monitor the amount of fluid in your womb around your baby. You should not take NSAIDs after about 30 weeks of pregnancy.
- are breastfeeding or plan to breast feed.

Tell your healthcare provider about all of the medicines you take, including prescription or over-the-counter medicines, vitamins or herbal supplements. NSAIDs and some other medicines can interact with each other and cause serious side effects. Do not start taking any new medicine without talking to your healthcare provider first.

What are the possible side effects of NSAIDs?

NSAIDs can cause serious side effects, including:

See “What is the most important information I should know about medicines called Nonsteroidal Anti-Inflammatory Drugs (NSAIDs)?”

- new or worse high blood pressure
- heart failure
- liver problems including liver failure
- kidney problems including kidney failure
- low red blood cells (anemia)
- life-threatening skin reactions
- life-threatening allergic reactions
- Other side effects of NSAIDs include: stomach pain, constipation, diarrhea, gas, heartburn, nausea, vomiting, and dizziness.

Get emergency help right away if you get any of the following symptoms:

- shortness of breath or trouble breathing
- chest pain
- weakness in one part or side of your body
- slurred speech
- swelling of the face or throat.

Stop taking your NSAID and call your healthcare provider right away if you get any of the following symptoms:

- nausea
- more tired or weaker than usual
- diarrhea
- itching
- your skin or eyes look yellow
- indigestion or stomach pain
- flu-like symptoms
- vomit blood
- there is blood in your bowel movement or it is black and sticky like tar
- unusual weight gain
- skin rash or blisters with fever
- swelling of the arms, legs, hands and feet.

If you take too much of your NSAID, call your healthcare provider or get medical help right away.

These are not all the possible side effects of NSAIDs. For more information, ask your healthcare provider or pharmacist about NSAIDs.

Call your doctor for medical advice about side effects. You may report side effects to FDA at 1-800-FDA-1088.

Other information about NSAIDs

- Aspirin is an NSAID but it does not increase the chance of a heart attack. Aspirin can cause bleeding in the brain, stomach, and intestines. Aspirin can also cause ulcers in the stomach and intestines.
- Some NSAIDs are sold in lower doses without a prescription (over-the-counter). Talk to your healthcare provider before using over-the-counter NSAIDs for more than 10 days.

General information about the safe and effective use of NSAIDs

Medicines are sometimes prescribed for purposes other than those listed in a Medication Guide. Do not use NSAIDs for a condition for which it was not prescribed. Do not give NSAIDs to other people, even if they have the same symptoms that you have. It may harm them.

If you would like more information about NSAIDs, talk with your healthcare provider. You can ask your pharmacist or healthcare provider for information about NSAIDs that is written for health professionals.

Distributed by: PuraCap Laboratories, LLC

DBA Blu Pharmaceuticals, Greenvale, NY 11548

For more information, go to www.puracaplabs.com or call 1-888-374-2791.

This Medication Guide has been approved by the U.S. Food and Drug Administration.

Rev. 05-2022-00

OE2624

PACKAGE/LABEL PRINCIPAL DISPLAY PANEL – 150 mg

Sulindac Tablets USP, 150 mg

PHARMACIST: Dispense the accompanying Medication Guide to each patient.

Rx Only

500 Tablets

PACKAGE/LABEL PRINCIPAL DISPLAY PANEL – 200 mg

Sulindac Tablets USP, 200 mg

PHARMACIST: Dispense the accompanying Medication Guide to each patient.

Rx Only

100 Tablets